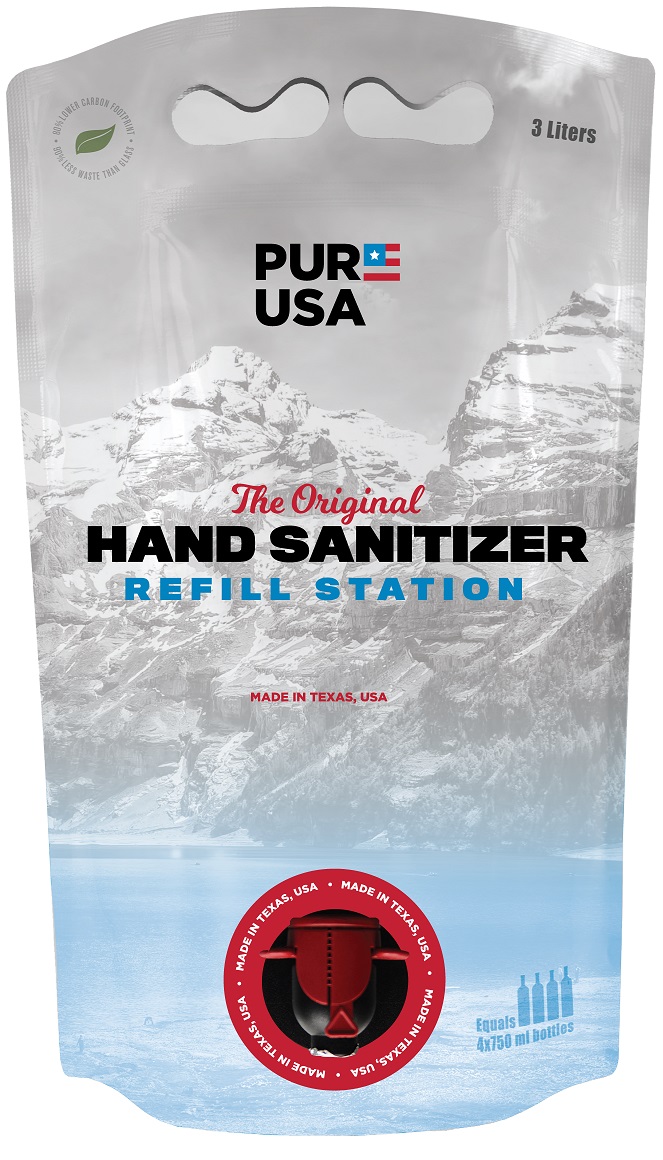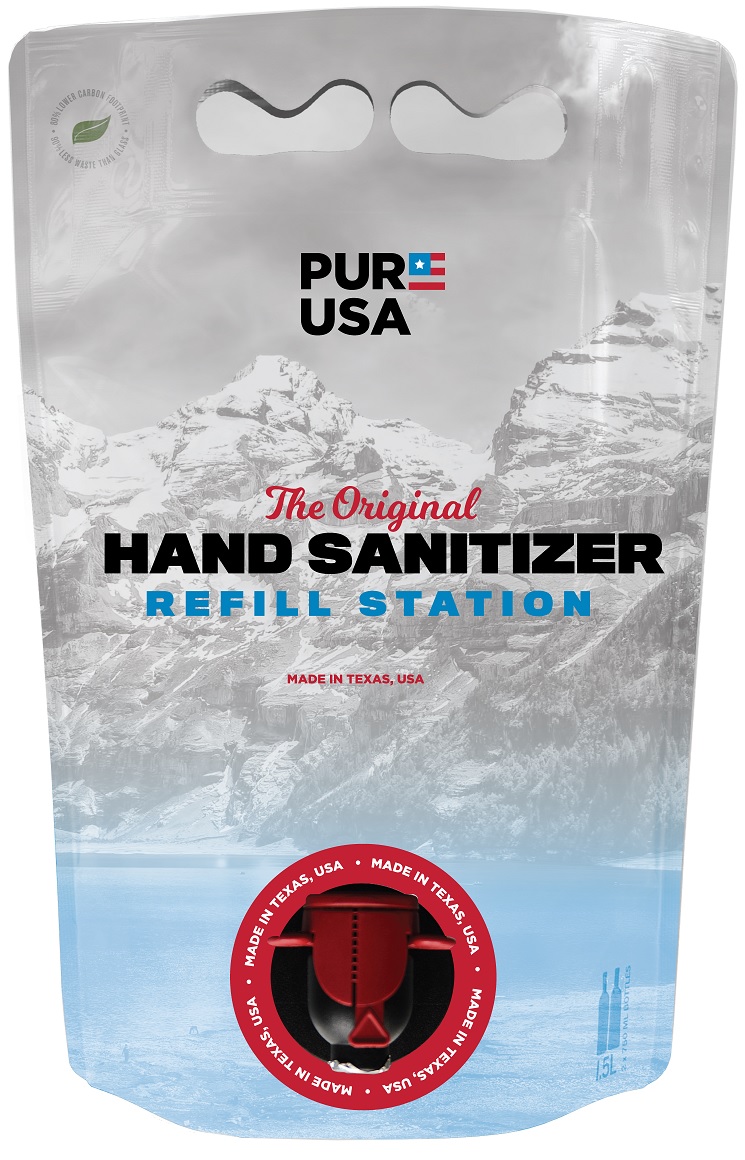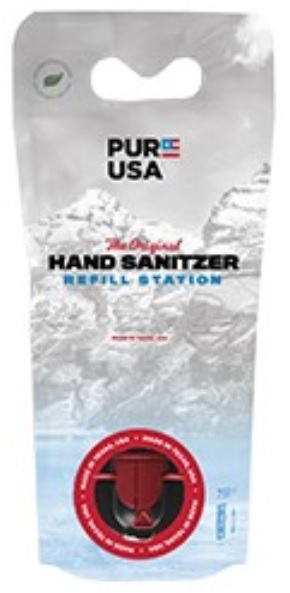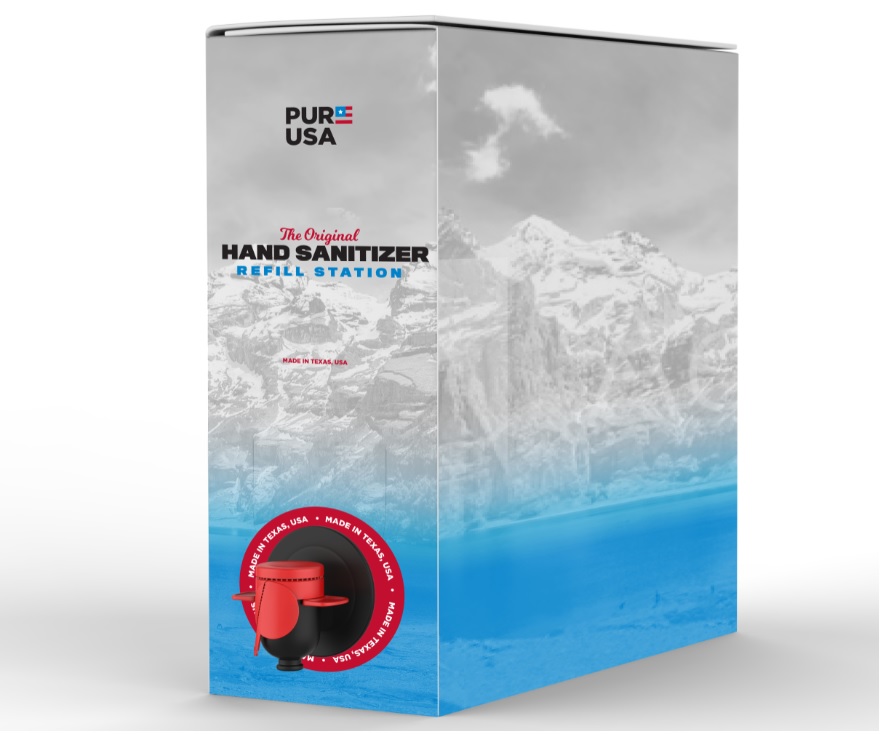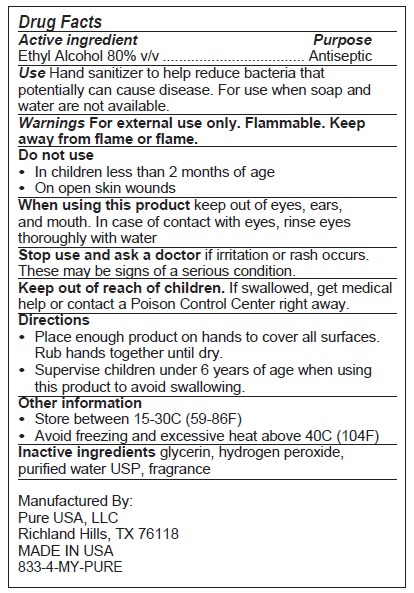 DRUG LABEL: Pure USA Hand Sanitizer
NDC: 80665-101 | Form: LIQUID
Manufacturer: Pure USA, LLC
Category: otc | Type: HUMAN OTC DRUG LABEL
Date: 20200928

ACTIVE INGREDIENTS: ALCOHOL 80 L/100 L
INACTIVE INGREDIENTS: GLYCERIN; HYDROGEN PEROXIDE; WATER

PURE USA The Original HAND SANITIZER

Active ingredient

Ethyl Alcohol 80% v/v

Purpose

Antiseptic

INDICATIONS AND USAGE

Use Hand sanitizer to help reduce bacteria that potentially can cause disease. For use when soap and water are not available.

WARNINGS

Warnings For external use only. Flammable. Keep away from flame or flame.

Do not use
• In children less than 2 months of age
• On open skin wounds

When using this product keep out of eyes, ears, and mouth. In case of contact with eyes, rinse eyes thoroughly with water

Stop use and ask a doctor if irritation or rash occurs. These may be signs of a serious condition.

Keep out of reach of children. If swallowed, get medical help or contact a Poison Control Center right away.

Directions

• Place enough product on hands to cover all surfaces. Rub hands together until dry.
• Supervise children under 6 years of age when using this product to avoid swallowing.

Other information

• Store between 15-30C (59-86F)
• Avoid freezing and excessive heat above 40C (104F)

INACTIVE INGREDIENT

Inactive ingredients glycerin, hydrogen peroxide, purified water USP, fragrance

Manufactured By:

Pure USA, LLC

Richand Hills, TX 76118

MADE IN USA

833-4-MY-PURE